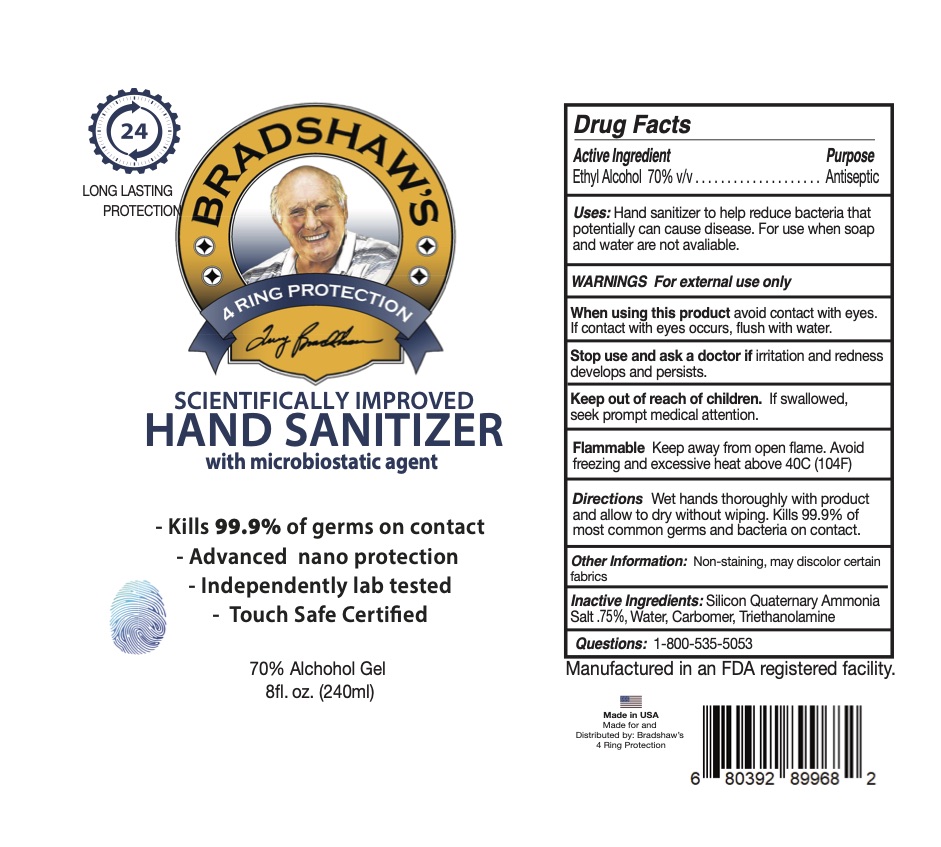 DRUG LABEL: Hand Sanitizer with Additive
NDC: 58418-119 | Form: GEL
Manufacturer: Tropical Enterprises International, Inc.
Category: otc | Type: HUMAN OTC DRUG LABEL
Date: 20201231

ACTIVE INGREDIENTS: ALCOHOL 20.4 mL/30 mL
INACTIVE INGREDIENTS: WATER; CARBOMER 1342; TROLAMINE; OCTADECYLDIMETHYL(3-TRIHYDROXYSILYLPROPYL)AMMONIUM CHLORIDE

Formula # HM4005-01 70% Ethyl Alcohol Hand Sanitizer Gel with Spar additive.

Active Ingredient

Ethyl Alcohol 70% v/v

Stop use and ask a doctor if irritation and redness develops and persists.

Keep out of reach of children: If swallowed, seek prompy medical attention.

PURPOSE

Uses: Hand sanitizer to help reduce bacteria that potentially can cause disease. For use when soap and water are not available.

Questions: 1-800-535-5053

DOSAGE AND ADMINISTRATION

Directions: Wet hands thoroughly with product and allow to dry without wiping.

INACTIVE INGREDIENT

Inactive Ingredients: Silicon Quaternary Ammonia Salt .75%, Water, Carbomer, Triethanolamine

WARNINGS: For external use only

SAFE HANDLING WARNING

Flammable: Keep away from open flame. Avoid freezing and excessive heat about 40C.

Other information: Non-staining, may discolor certain fabrics.

INDICATIONS AND USAGE

Uses: For handwashing to decrease bacteria on the skin.

When using this product avoid contact with eyes. If contact with eyes occurs, flush with water.